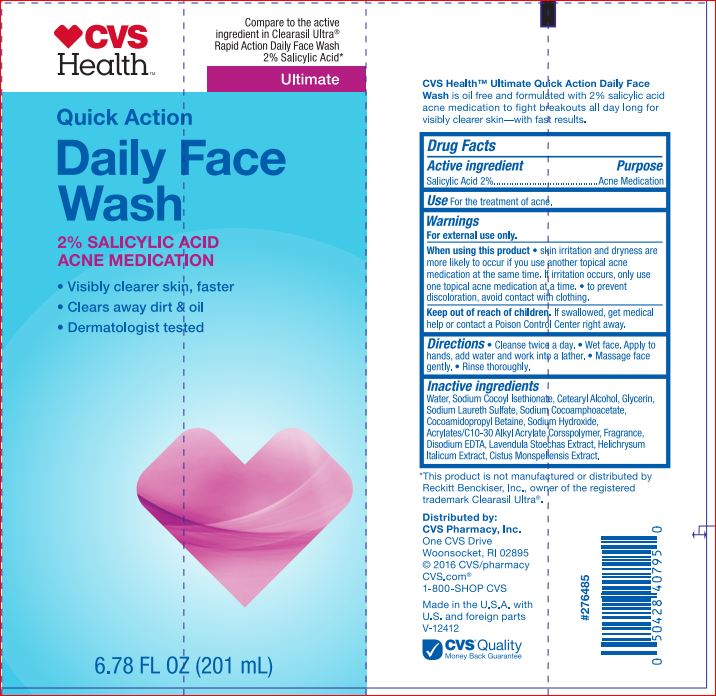 DRUG LABEL: Daily Face Wash
NDC: 59779-834 | Form: CREAM
Manufacturer: CVS
Category: otc | Type: HUMAN OTC DRUG LABEL
Date: 20171211

ACTIVE INGREDIENTS: Salicylic Acid 2 g/100 mL
INACTIVE INGREDIENTS: WATER; Sodium Cocoyl Isethionate; CETOSTEARYL ALCOHOL; Glycerin; Sodium Laureth Sulfate; Sodium Hydroxide; CARBOMER INTERPOLYMER TYPE A (ALLYL SUCROSE CROSSLINKED); EDETATE DISODIUM; LAVANDULA STOECHAS FLOWERING TOP; HELICHRYSUM ITALICUM FLOWER

Drug Facts

Active ingredient Purpose
Salicylic Acid 2%.........................................Acne Medication

INDICATIONS AND USAGE

Use For the treatment of acne.

Warnings For external use only.

When using this product • skin irritation and dryness are more likely to occur if you use another topical acne medication at the same time. If irritation occurs, only use one topical acne medication at a time. • to prevent discoloration, avoid contact with clothing

Keep out of reach of children. If swallowed, get medical help or contact a Poison Control Center right away.

DOSAGE AND ADMINISTRATION

Directions • Cleanse twice a day. • Wet face. Apply to hands, add water and work into a lather. • Massage face gently. • Rinse thoroughly.

Inactive ingredients
Water, Sodium Cocoyl Isethionate, Cetearyl Alcohol, Glycerin, Sodium Laureth Sulfate, Sodium Cocoamphoacetate, Cocoamidopropyl Betaine, Sodium Hydroxide, Acrylates/C10-30 Alkyl Acrylate Corsspolymer, Fragrance, Disodium EDTA, Lavendula Stoechas Extract, Helichrysum Italicum Extract, Cistus Monspeliensis Extract.